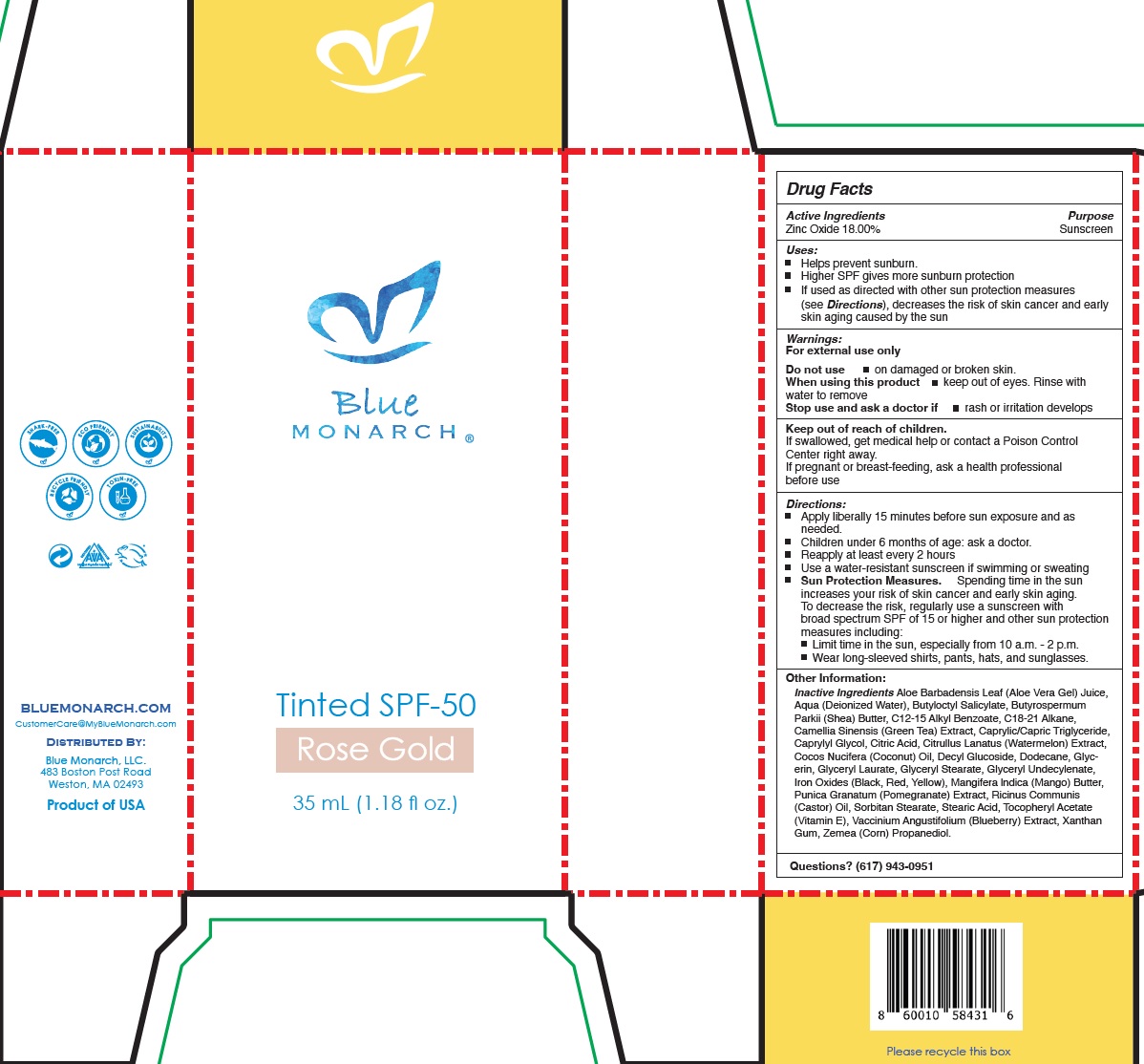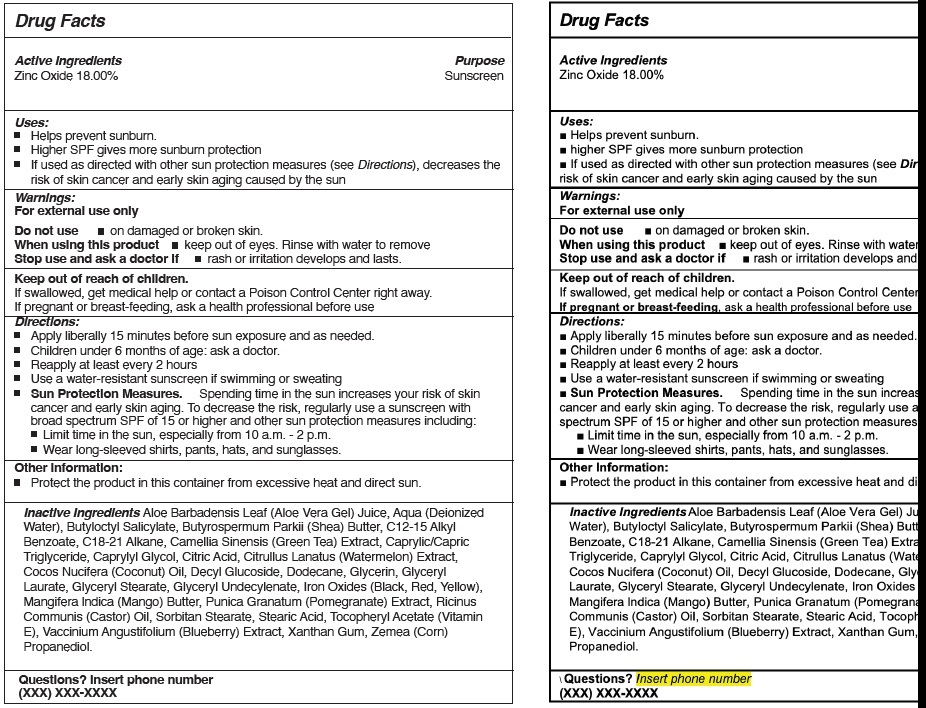 DRUG LABEL: BLUE MONARCH Tinted SPF-50 (Rose Gold)
NDC: 72101-419 | Form: CREAM
Manufacturer: Blue Monarch, LLC
Category: otc | Type: HUMAN OTC DRUG LABEL
Date: 20231111

ACTIVE INGREDIENTS: ZINC OXIDE 180 mg/1 mL
INACTIVE INGREDIENTS: ALOE VERA LEAF; WATER; BUTYLOCTYL SALICYLATE; SHEA BUTTER; ALKYL (C12-15) BENZOATE; C18-C21 ALKANE; GREEN TEA LEAF; MEDIUM-CHAIN TRIGLYCERIDES; CAPRYLYL GLYCOL; CITRIC ACID MONOHYDRATE; WATERMELON; COCONUT OIL; DECYL GLUCOSIDE; DODECANE; GLYCERIN; GLYCERYL LAURATE; GLYCERYL MONOSTEARATE; FERRIC OXIDE RED; MANGO; PUNICA GRANATUM ROOT BARK; CASTOR OIL; SORBITAN MONOSTEARATE; STEARIC ACID; .ALPHA.-TOCOPHEROL ACETATE; BLUEBERRY; XANTHAN GUM; CORN

BLUE MONARCH Tinted SPF-50 (Rose Gold)

Active Ingredients

Zinc Oxide 18.00%

Purpose

Sunscreen

Uses:

- Helps prevent sunburn.
- Higher SPF gives more sunburn protection
- If used as directed with other sun protection measures (see Directions), decreases the risk of skin cancer and early skin aging caused by the sun

Warnings:

For external use only

Do not use

- on damaged or broken skin.

When using this product

- keep out of eyes. Rinse with water to remove

Stop use and ask a doctor if

- rash or irritation developsand

Keep out of reach of children.

If swallowed, get medical help or contact a Poison Control Center right away.

If pregnant or breast-feeding,

ask a health professional before use

Directions:

- Apply liberally 15 minutes before sun exposure and as needed.
- Children under 6 months of age: ask a doctor.
- Reapply at least every 2 hours
- Use a water-resistant sunscreen if swimming or sweating
- Spending time in the sun increases your risk of skin cancer and early skin aging. To decrease the risk, regularly use a sunscreen with broad spectrum SPF of 15 or higher and other sun protection measures including: Sun Protection Measures.
- Limit time in the sun, especially from 10 a.m. - 2 p.m.
- Wear long-sleeved shirts, pants, hats, and sunglasses.

Other Information:

- Protect the product in this container from excessive heat and direct sun.

Inactive Ingredients

Aloe Barbadensis Leaf (Aloe Vera Gel) Juice, Aqua (Deionized Water), Butyloctyl Salicylate, Butyrospermum Parkii (Shea) Butter, C12-15 Alkyl Benzoate, C18-21 Alkane, Camellia Sinensis (Green Tea) Extract, Caprylic/Capric Triglyceride, Caprylyl Glycol, Citric Acid, Citrullus Lanatus (Watermelon) Extract, Cocos Nucifera (Coconut) Oil, Decyl Glucoside, Dodecane, Glycerin, Glyceryl Laurate, Glyceryl Stearate, Glyceryl Undecylenate, Iron Oxides (Black, Red, Yellow), Mangifera lndica (Mango) Butter, Punica Granatum (Pomegranate) Extract, Ricinus Communis (Castor) Oil, Sorbitan Stearate, Stearic Acid, Tocopheryl Acetate (Vitamin E), Vaccinium Angustifolium (Blueberry) Extract, Xanthan Gum, Zemea (Corn) Propanediol.

Questions?

(617) 943-0951